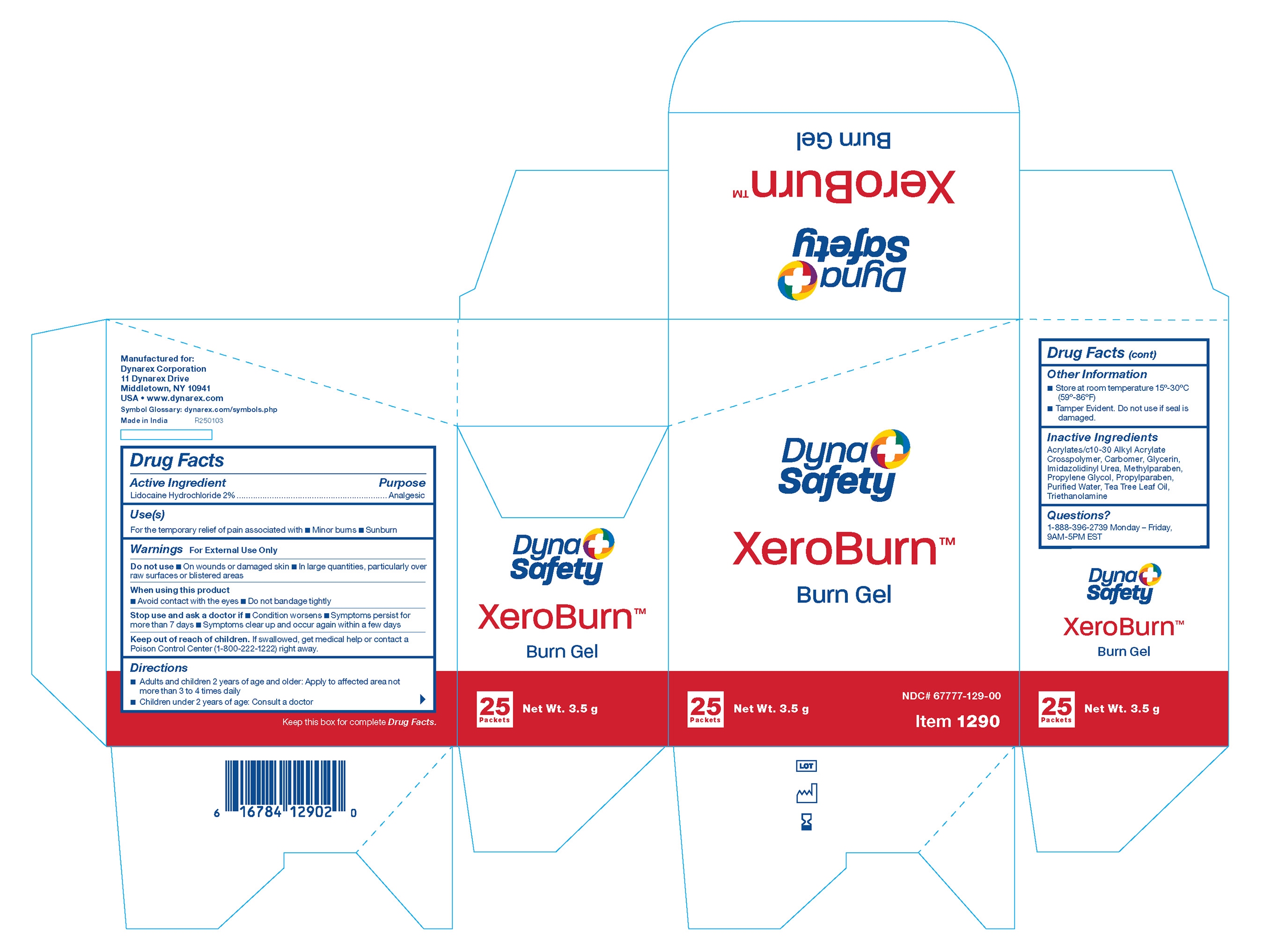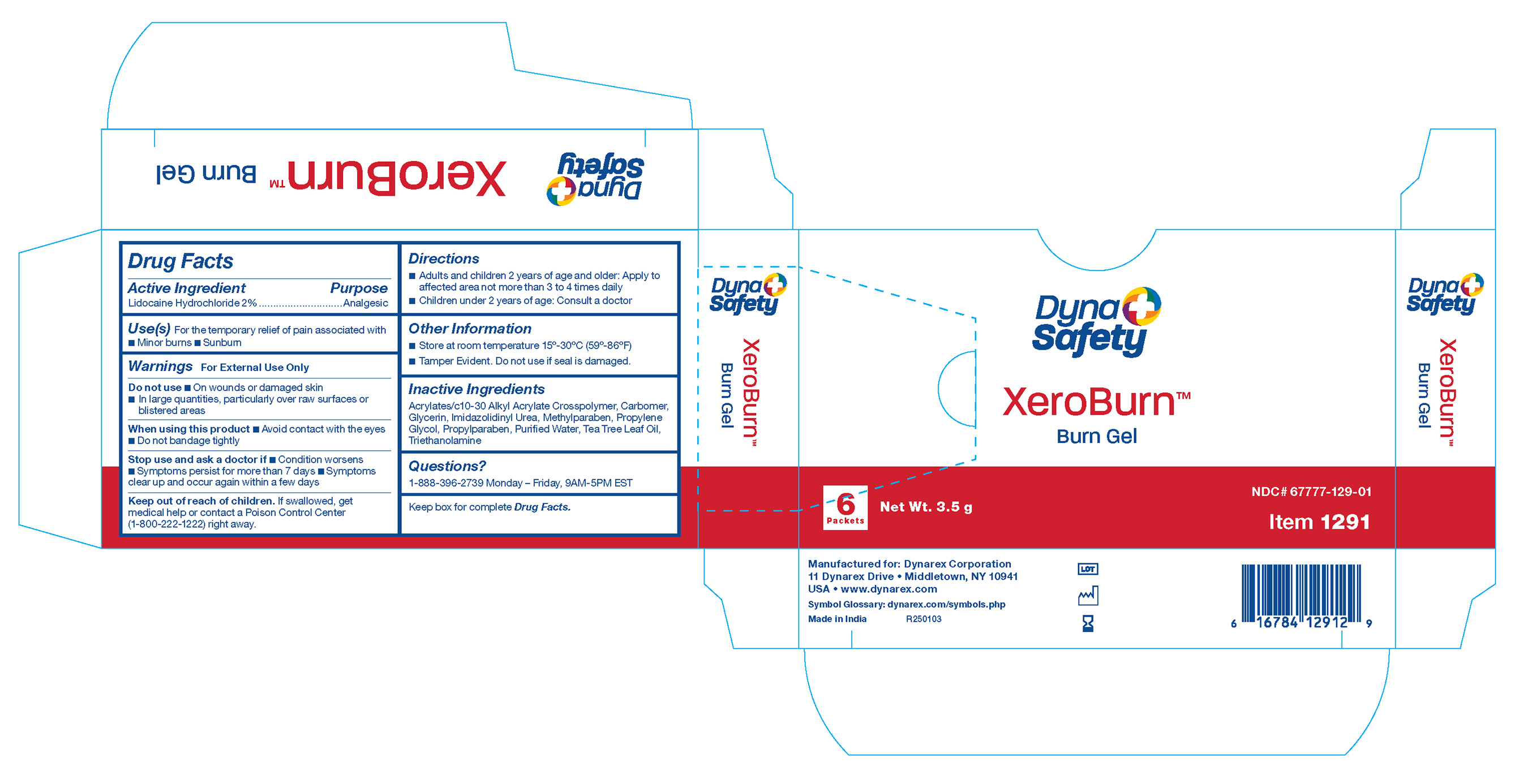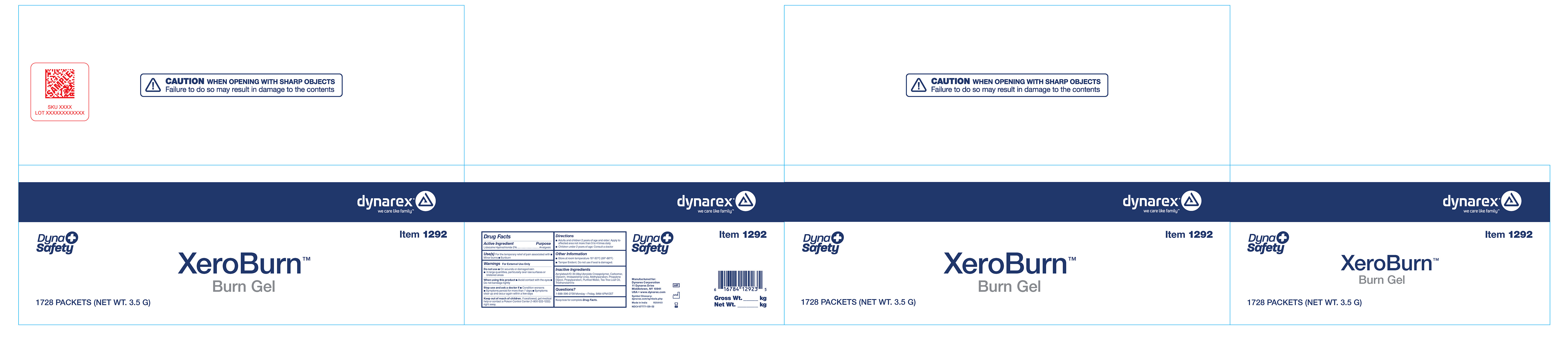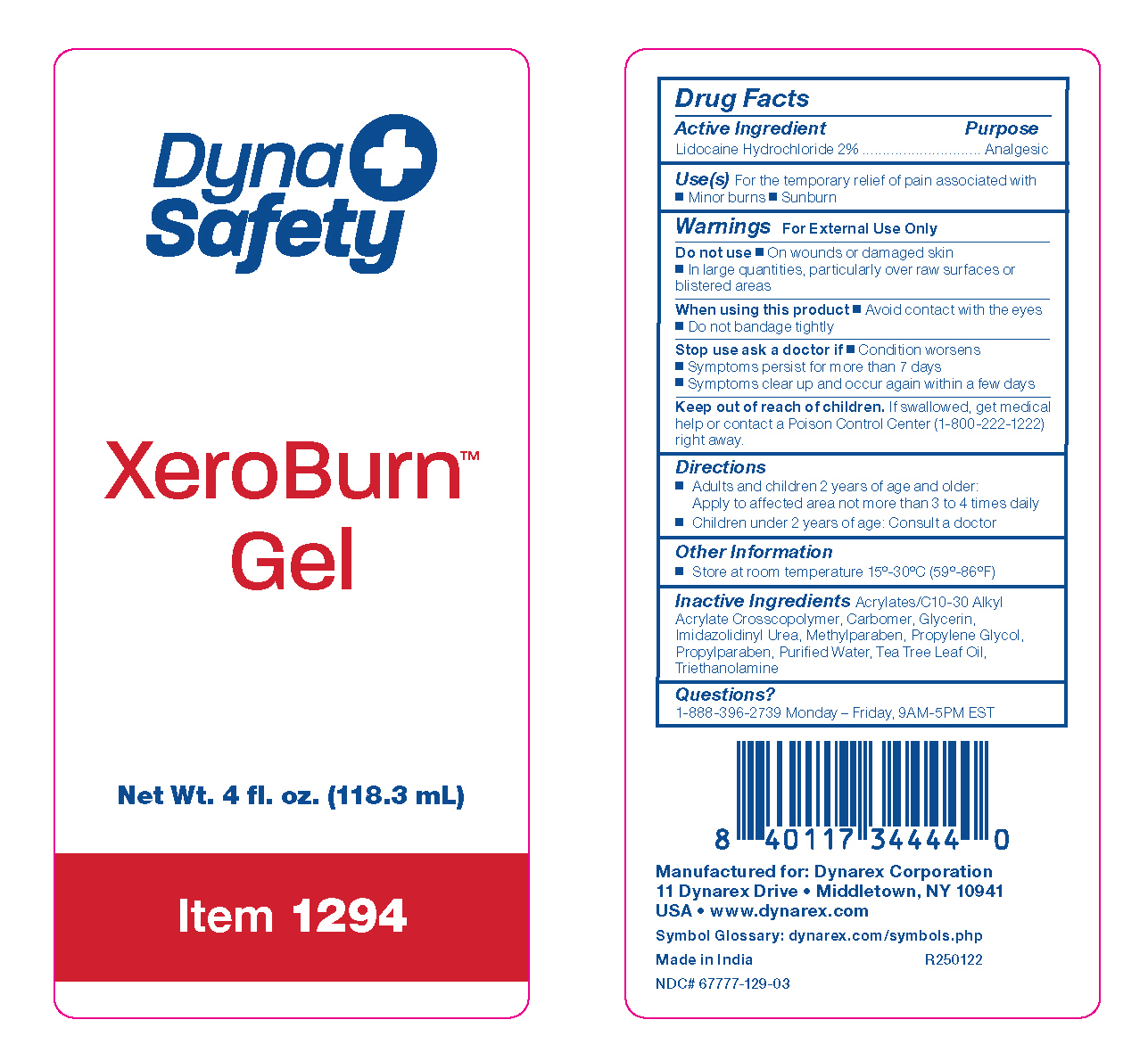 DRUG LABEL: XeroBurn Burn Gel
NDC: 67777-129 | Form: GEL
Manufacturer: Dynarex Corporation
Category: otc | Type: HUMAN OTC DRUG LABEL
Date: 20250313

ACTIVE INGREDIENTS: LIDOCAINE HYDROCHLORIDE 2 g/100 g
INACTIVE INGREDIENTS: TROLAMINE; METHYLPARABEN; GLYCERIN; IMIDUREA; PROPYLENE GLYCOL; PROPYLPARABEN; WATER; TEA TREE OIL; CARBOMER HOMOPOLYMER TYPE C (ALLYL PENTAERYTHRITOL CROSSLINKED); CARBOMER COPOLYMER TYPE B (ALLYL PENTAERYTHRITOL CROSSLINKED)

1290 XeroBurn Burn Gel 67777-129-00
1291 XeroBurn Burn Gel 67777-129-01
1292 XeroBurn Burn Gel 67777-129-02
1294 XeroBurn Burn Gel 67777-129-03

Active Ingredient

Lidocaine Hydrochloride 2%

Purpose

Analgesic

Use(s)

■ For the temporary relief of pain associated with ■ Minor burns ■ Sunburn

■ Provides cooling pain relief

Warnings

For External Use Only

Do not use

■ On wounds or damaged skin

■ In large quantities, particularly over raw surfaces or blistered areas

When using this product

■ Avoid contact with the eyes

■ Do not bandage tightly

Stop use and ask a doctor if

■ Condition worsens

■ Symptoms persist for more than 7 days

■ Symptoms clear up and occur again within a few days

Keep out of reach of children

If swallowed, get medical help or contact a Poison Control Center (1-800-222-1222) right away.

Directions

■ Adults and children 2 years of age and older: Apply to affected area not more than 3 to 4 times daily

■ Children under 2 years of age: Consult a doctor

Other Information

• Store at room temperature 15º-30ºC (59º-86ºF)

• Tamper Evident. Do not use if seal is damaged.

Inactive Ingredients

Acrylates/C10-30 Alkyl Acrylate Crosscopolymer, Carbomer, Glycerin, Imidazolidinyl Urea, Methylparaben, Propylene Glycol, Propylparaben, Purified Water, Tea Tree Leaf Oil, Triethanolamine

Questions?

1-888-396-2739 Monday - Friday, 9AM - 5PM EST

Label

XeroBurn Burn Gel

Label

XeroBurn Burn Gel 1290

Label

XeroBurn Burn Gel 1291

Label

XeroBurn Burn Gel 1292